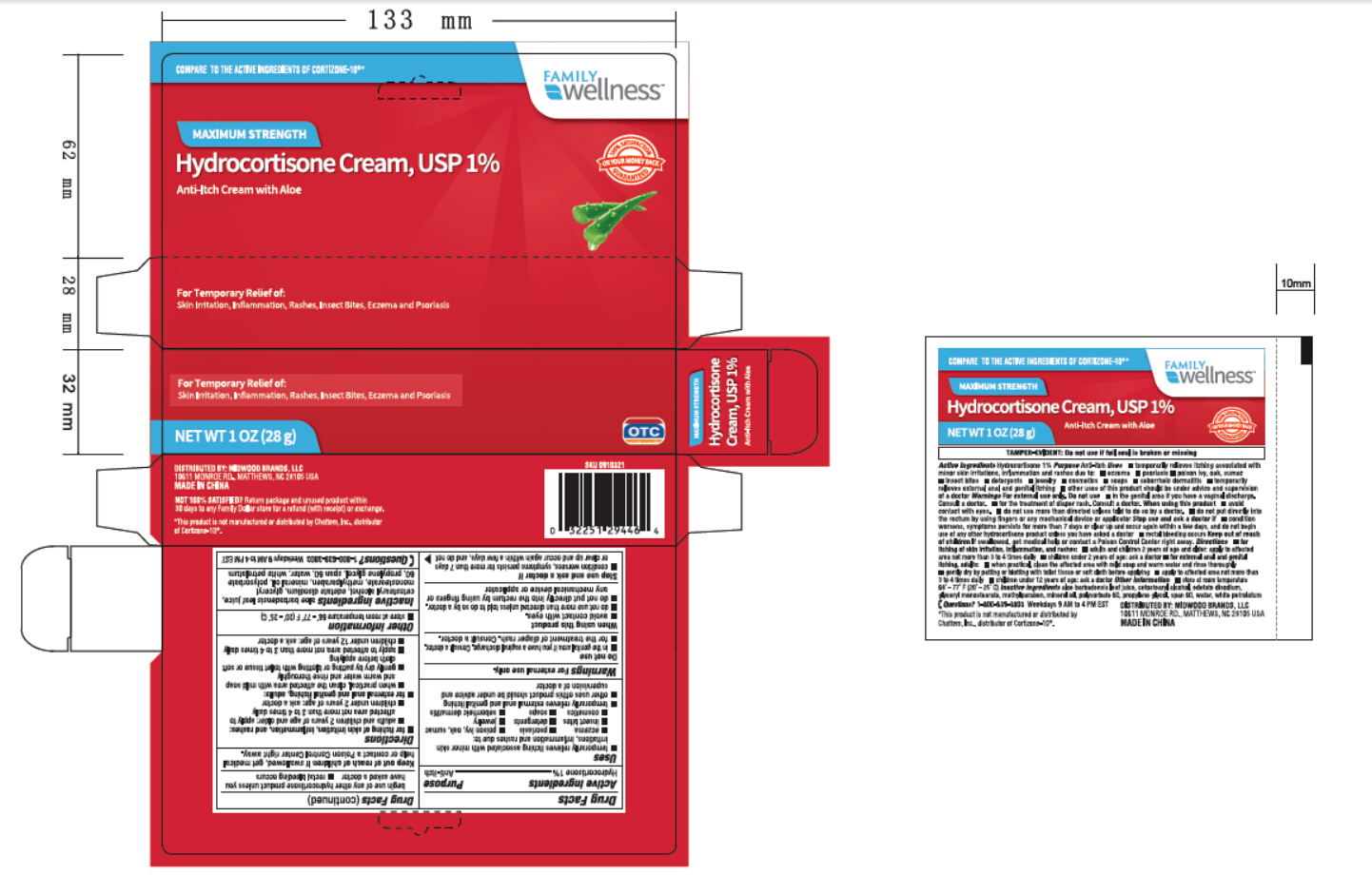 DRUG LABEL: Family Wellness
NDC: 69571-009 | Form: CREAM
Manufacturer: FRONT PHARMACEUTICAL PLC
Category: otc | Type: HUMAN OTC DRUG LABEL
Date: 20231027

ACTIVE INGREDIENTS: HYDROCORTISONE 1 g/100 g
INACTIVE INGREDIENTS: ALOE VERA LEAF; CETOSTEARYL ALCOHOL; EDETATE DISODIUM; GLYCERYL MONOSTEARATE; METHYLPARABEN; MINERAL OIL; POLYSORBATE 60; PROPYLENE GLYCOL; SORBITAN MONOSTEARATE; WATER; PETROLATUM

Active ingredients

Hydrocortisone 1%

Purpose

Anti-itch

Uses

•temporarily relieves itching associated with minor skin

irritations, inflammation and rashes due to:

•eczema •psoriasis •poison ivy, oak, sumac

•insect bites •detergents •jewelry

•cosmetics •soaps •saborrheiic dermatitis

•temproarily relieves external and genital itching

•other uses of this product should be under advice and

supervision of a doctor

Warnings For external use only.

: Do not use

•in the genital area if you have vaginal discharge. Consult a doctor.

•for the treatment of diaper rash. Consult a doctor.

: When using this product

•avoid contact with eyes.

•do not use more than directed unless told to do so by a doctor.

•do not put directly into rectum by using fingers or

any mechanical device or applicator.

Stop use and ask a doctor if

•condition worsens, symptoms persist for more than 7 days

or clear up and occur again within a few days, and do not

begin use of any other hydrocortisone product unless you

have asked a doctor •rectal bleeding occurs

KEEP OUT OF REACH OF CHILDREN

. If swallowed, get medical Keep out of reach of children

help or contact a Poison Control Center right away.

Directions

•for itching or skin irritation, inflammation and rashes:

•adults and children 2 years of age and older: apply to

affected area not more than 3 to 4 times daily

•children under 2 years of age: ask a doctor

•for external and genital itching, adults:

•when practical, clean the affected area with mild soap

and warm waterand rinse thoroughly

•gently dry by patting or blotting with toilet tissue or soft

cloth before applying

•apply to affected area not more than 3 to 4 times daily

•children under 12 years of age: ask a doctor

Other information

•store at room temperature 68° - 77° F (20° - 25° C)

aloe barbadensis leaf juice, Inactive ingredients

ceteastrearyl alcohol, edetate disodium, glyceryl

monostearate, methylparaben, mineral oil, polysorbate

60, propylene glycol, span 60, water, white petrolatum

QUESTIONS

1-800-638-3800 Weekdays 0 AM to 4 PM EST Questions?